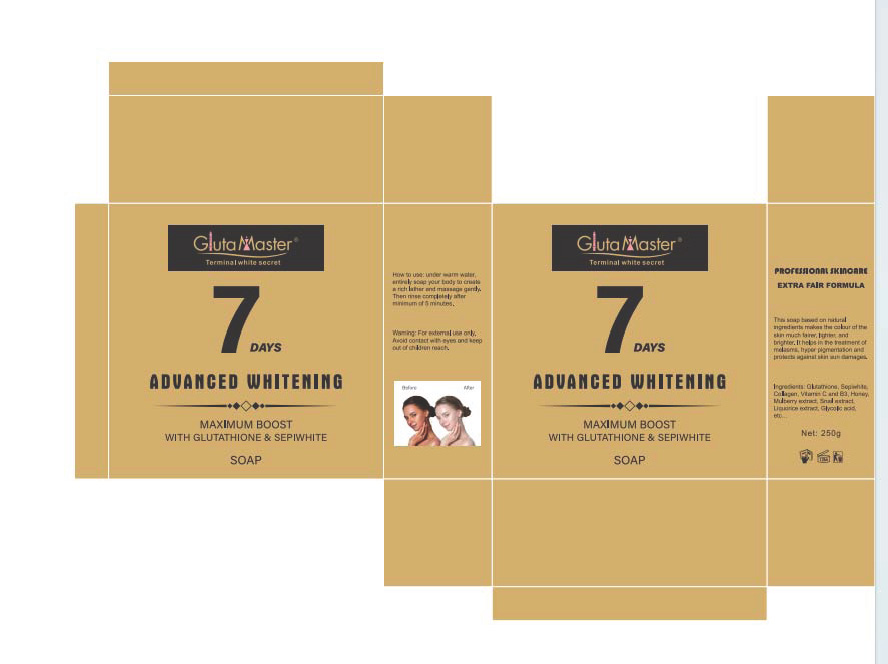 DRUG LABEL: 7 DAYS ADVANCED WHITENINGSOAP
NDC: 84423-052 | Form: SOAP
Manufacturer: Guangzhou Kadiya Biotechnology Co., Ltd.
Category: otc | Type: HUMAN OTC DRUG LABEL
Date: 20241003

ACTIVE INGREDIENTS: GLUTATHIONE 0.25 g/250 g; GOLD 0.025 g/250 g; COCONUT OIL 0.25 g/250 g
INACTIVE INGREDIENTS: GLYCERIN; WATER; MALTITOL; MANNITOL; PROPYLENE GLYCOL; LAURIC ACID; SODIUM LAURETH SULFATE; SODIUM HYDROXIDE; COCO/OLEAMIDOPROPYL BETAINE; SHEA BUTTER; SORBITOL; SUCROSE; STEARIC ACID; ALCOHOL; OLIVE OIL

PURPOSE

For skin cleansing, exfoliation and whitening moisturization

INACTIVE INGREDIENT

GLYCERIN，WATER，SORBITOL，MALTITOL，MANNITOL，PROPYLENE GLYCOL，WHITE SUGAR，LAURIC ACID，SODIUM LAURETH SULFATE，STEARIC ACID ，SODIUM HYDROXIDE，COCAMIDOPYOPY IBETAINE，ETHYL ALCOHOL，OLEAEUROPAEA(OLIVE)FRUIT OLL，BUTYROSPERMUMPARKII(SHEA)BUTTER，AROMA

WARNINGS

1、For external use only, avoid contact with eyes when used
2、Keep out of reach of children

INDICATIONS AND USAGE

For skin cleansing, exfoliation and whitening moisturization

DOSAGE AND ADMINISTRATION

For skin cleansing, exfoliation and whitening moisturization

KEEP OUT OF REACH OF CHILDREN SECTION

Active Ingredients
Glutathione0.1%
COCOS NUCIFERA(COCONUT)OIL0.1%
Gold0.01%

KEEP OUT OF REACH OF CHILDREN SECTION

PACKAGE LABEL

Active Ingredients
Glutathione0.1%
COCOS NUCIFERA(COCONUT)OIL0.1%
Gold0.01%

Uses：
For skin cleansing, exfoliation and whitening moisturization
The storage method：
Store sealed in a cool place and out of sunlight

Warning.
1、For external use only, avoid contact with eyes when used
2、Keep out of reach of children

Inactive ingredients：
GLYCERIN，WATER，SORBITOL，MALTITOL，MANNITOL，PROPYLENE GLYCOL，WHITE SUGAR，LAURIC ACID，SODIUM LAURETH SULFATE，STEARIC ACID ，SODIUM HYDROXIDE，COCAMIDOPYOPY IBETAINE，ETHYL ALCOHOL，OLEAEUROPAEA(OLIVE)FRUIT OLL，BUTYROSPERMUMPARKII(SHEA)BUTTER，AROMA